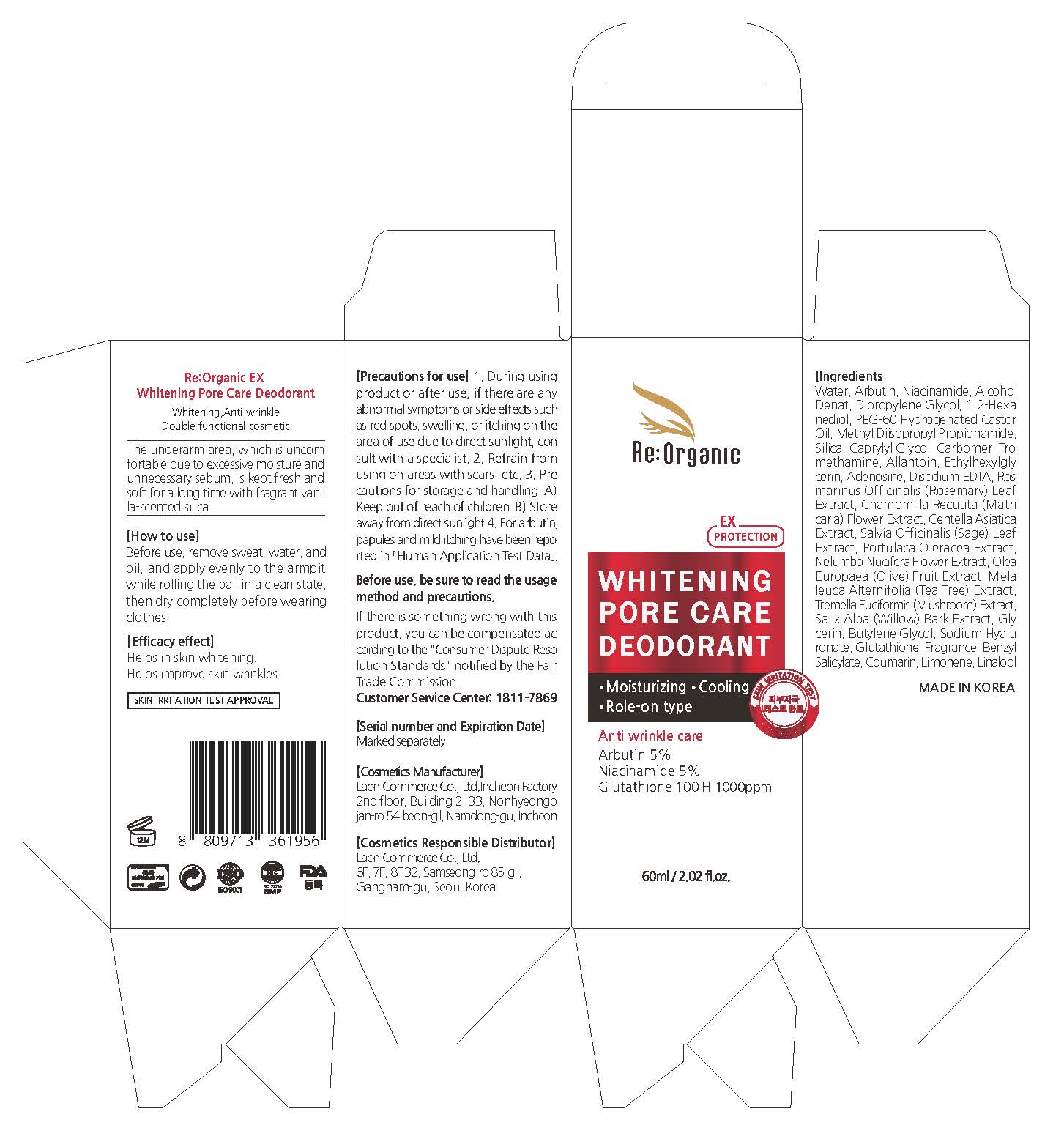 DRUG LABEL: Reoganic EX Whitening Pore Care Deodorant
NDC: 82083-0025 | Form: LIQUID
Manufacturer: LAON COMMERCE co ltd
Category: otc | Type: HUMAN OTC DRUG LABEL
Date: 20230922

ACTIVE INGREDIENTS: NIACINAMIDE 5 g/100 mL; ADENOSINE 0.04 g/100 mL; ARBUTIN 5 g/100 mL
INACTIVE INGREDIENTS: WATER; HYALURONATE SODIUM

ACTIVE INGREDIENT

Arbutin, Niacinamide, Adenosine

INACTIVE INGREDIENT

Water
Alcohol Denat
Dipropylene Glycol
1,2-Hexanediol
PEG-60 Hydrogenated Castor Oil
Methyl Diisopropyl Propionamide
Silica
Caprylyl Glycol
Carbomer
Tromethamine
Allantoin
Ethylhexylglycerin
Disodium EDTA
Rosmarinus Officinalis (Rosemary) Leaf Extract
Chamomilla Recutita (Matricaria) Flower Extract
Centella Asiatica Extract
Salvia Officinalis (Sage) Leaf Extract
Portulaca Oleracea Extract
Nelumbo Nucifera Flower Extract
Olea Europaea (Olive) Fruit Extract
Melaleuca Alternifolia (Tea Tree) Extract
Tremella Fuciformis (Mushroom) Extract
Salix Alba (Willow) Bark Extract
Glycerin
Butylene Glycol
Sodium Hyaluronate
Glutathione
Fragrance
Benzyl Salicylate
Coumarin
Limonene
Linalool

PURPOSE

skin protect

KEEP OUT OF REACH OF THE CHILDREN

INDICATIONS AND USAGE

Before use, remove sweat, water, and oil, and apply evenly to the armpit while rolling the ball in a clean state, then dry completely before wearing clothes.

WARNINGS

[Precautions for use]

1. During using product or after use, if there are any abnormal symptoms or side effects such as red spots, swelling, or itching on the area of use due to direct sunlight, con sult with a specialist. 2. Refrain from using on areas with scars, etc. 3. Pre cautions for storage and handling A) Keep out of reach of children B) Store away from direct sunlight 4. For arbutin, papules and mild itching have been repo rted in 「Human Application Test Data」.

DOSAGE AND ADMINISTRATION

topical use only